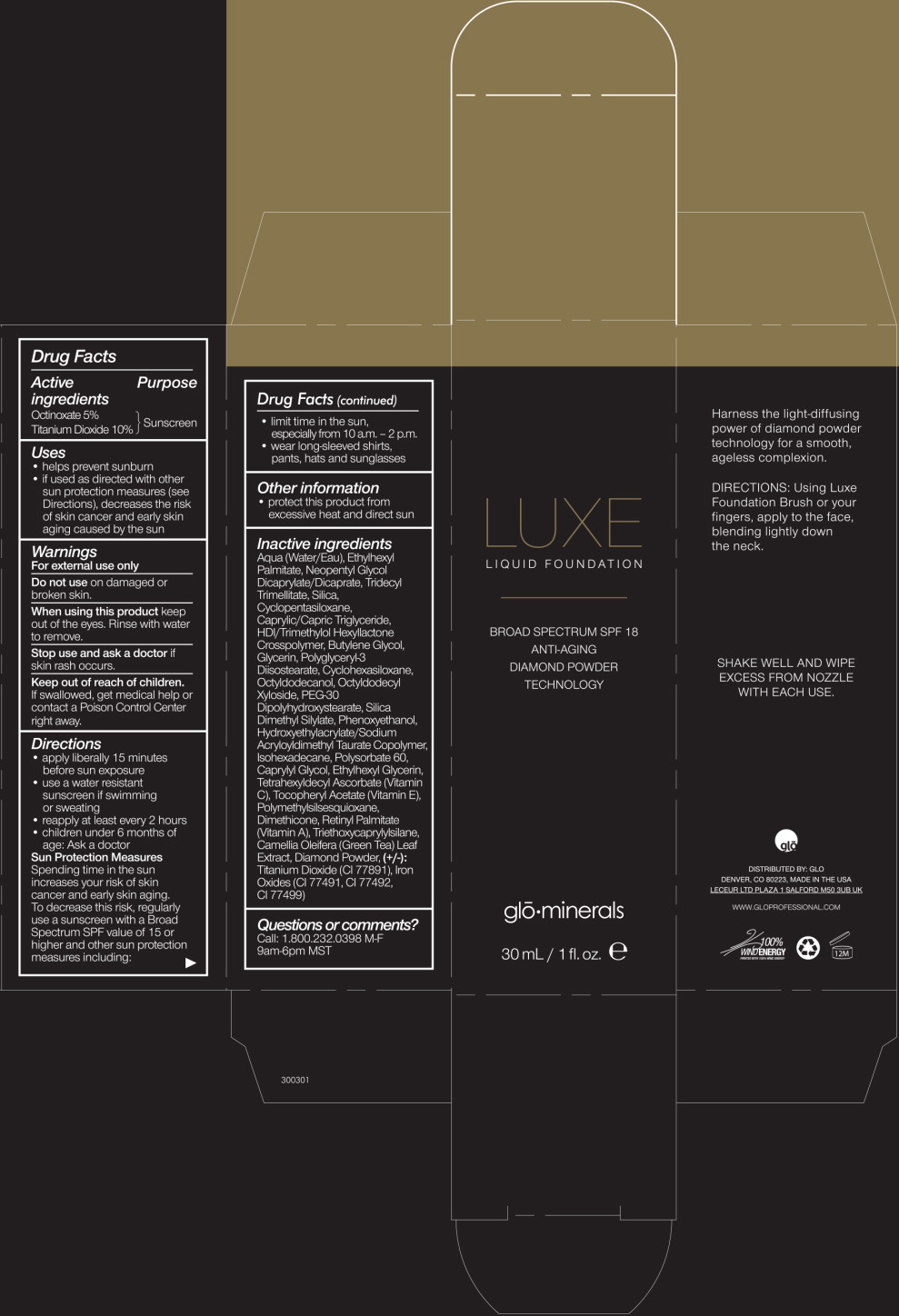 DRUG LABEL: Octinoxate
NDC: 60541-8407 | Form: LOTION
Manufacturer: Hayden Caleel LLC
Category: otc | Type: HUMAN OTC DRUG LABEL
Date: 20130827

ACTIVE INGREDIENTS: Octinoxate 0.05 g/1 mL
INACTIVE INGREDIENTS: Water; Ethylhexyl Palmitate; Neopentyl Glycol Dicaprylate/Dicaprate; Tridecyl Trimellitate; Silicon Dioxide; Medium-Chain Triglycerides; Cyclomethicone 6; Cyclomethicone 5; Butylene Glycol; Glycerin; Polyglyceryl-3 Diisostearate; Octyldodecanol; Peg-30 Dipolyhydroxystearate; Triethoxycaprylylsilane; Dimethicone; Phenoxyethanol; Silica Dimethyl Silylate; Caprylyl Glycol; Hydroxyethyl Acrylate/Sodium Acryloyldimethyl Taurate Copolymer (45000 Mpa.S At 1%); Isohexadecane; Polysorbate 60; Ethylhexylglycerin; .Alpha.-Tocopherol Acetate; Tetrahexyldecyl Ascorbate; Hexylene Glycol; Polymethylsilsesquioxane (4.5 Microns); Vitamin A Palmitate; Camellia Oleifera Leaf; Titanium Dioxide; Ferric Oxide Red

Drug Facts

Active ingredients

Octinoxate 5%

Titanium Dioxide 10%

Purpose

Sunscreen

Uses

- helps prevent sunburn
- if used as directed with other sun protection measures (see Directions), decreases the risk of skin cancer and early skin aging caused by the sun.

Warnings

For external use only

Do not use on damaged or broken skin.

When using this product keep out of the eyes. Rinse with water to remove.

Stop use and ask a doctor if skin rash occurs.

Keep out of reach of children. If swallowed, get medical help or contact a Poison Control Center right away.

Directions

- apply liberally 15 minutes before sun exposure
- use a water resistant sunscreen if swimming or sweating
- reapply at least every 2 hours
- children under 6 months of age: Ask a doctor

Sun Protection Measures

Spending time in the sun increases your risk of skin cancer and early skin aging. To decrease this risk, regularly use a sunscreen with a Broad Spectrum SPF value of 15 or higher and other sun protection measures including:

- limit time in the sun, especially from 10 a.m. – 2 p.m.
- wear long-sleeved shirts, pants, hats, and sunglasses

Other information

- protect this product from excessive heat and direct sun

Inactive ingredients

Aqua (Water/Eau), Ethylhexyl Palmitate, Neopentyl Glycol Dicaprylate/Dicaprate, Tridecyl Trimellitate, Silica, Cyclopentasiloxane, Caprylic/Capric Triglyceride, HDI/Trimethylol Hexyllactone Crosspolymer, Butylene Glycol, Glycerin, Polyglyceryl-3 Diisostearate, Cyclohexasiloxane, Octyldodecanol, Octyldecyl Xyloside, PEG-30 Dipolyhydroxystearate, Silica Dimethyl Silylate, Phenoxyethanol, Hydroxyethylacrylate/Sodium Acryloydimethyl Taurate Copolymer, Isohexadecane, Polysorbate 60, Caprylyl Glycol, Ethylhexyl Glycerin, Tetrahexyldecyl Ascorbate (Vitamin C), Tocopheryl Acetate (Vitamin E), Polymethylsilsesquioxane, Dimethicone, Retinyl Palmitate (Vitamin A), Triethoxycaprylylsilane, Camellia Oleifera (Green Tea) Leaf Extract, Diamond Powder, (+/-):Titanium Dioxide (CI 77891), Iron Oxides (CI 77491, CI 77492, CI 77499)

Questions or comments?

Call: 1.800.232.0398 M-F 9am-6pm MST

Principal Display Panel - 30 mL Carton Label

LUXE

LIQUID FOUNDATION

BROAD SPECTRUM SPF 18

ANTI-AGING

DIAMOND POWDER

TECHNOLOGY

glo·minerals

30 mL / 1 fl. oz.